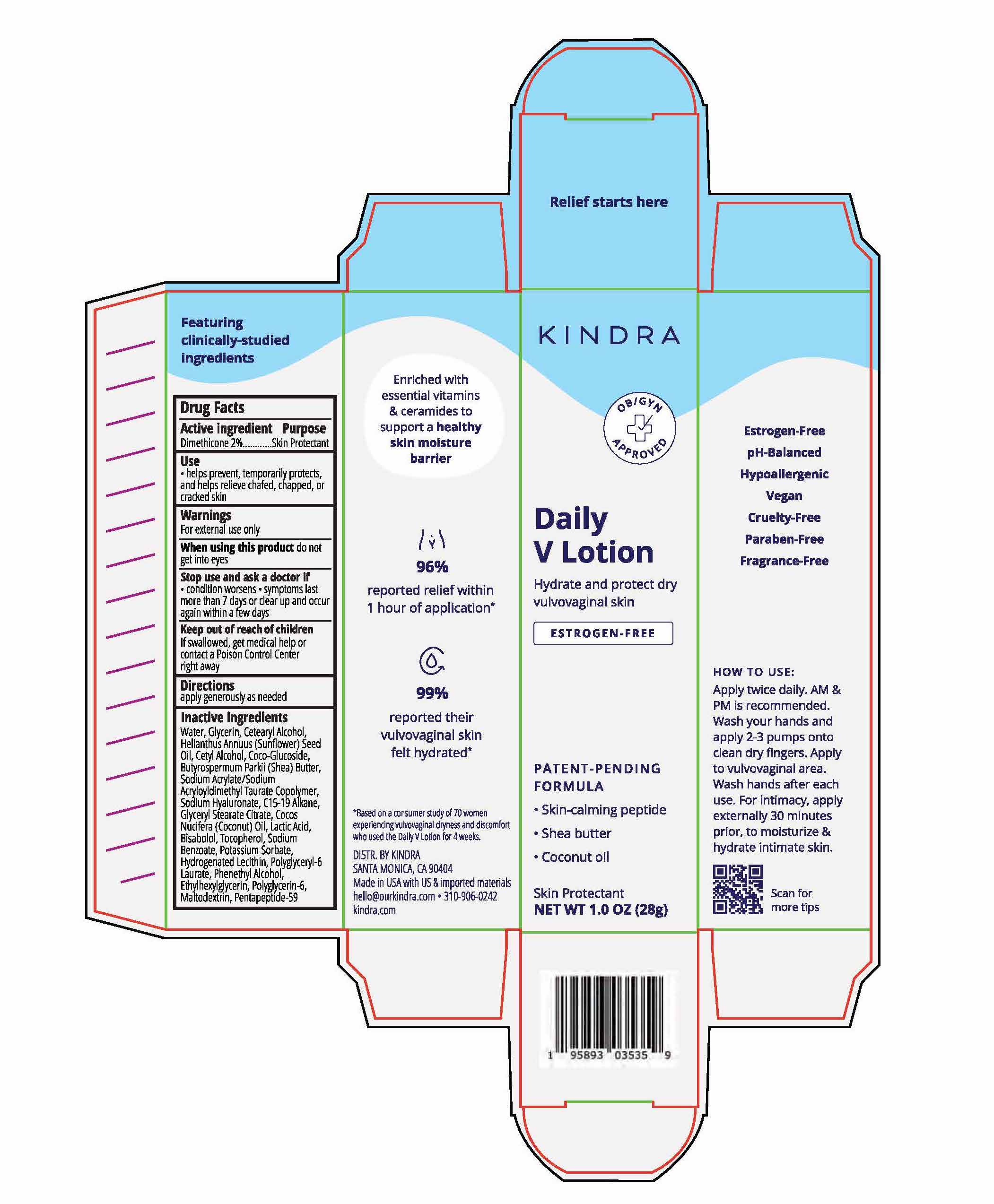 DRUG LABEL: Daily VLotion
NDC: 84528-359 | Form: LOTION
Manufacturer: Kindra
Category: otc | Type: HUMAN OTC DRUG LABEL
Date: 20260108

ACTIVE INGREDIENTS: DIMETHICONE 0.56 g/28 g
INACTIVE INGREDIENTS: COCONUT OIL; LACTIC ACID; WATER; CETOSTEARYL ALCOHOL; SUNFLOWER OIL; CETYL ALCOHOL; SHEA BUTTER; SODIUM ACRYLATE/SODIUM ACRYLOYLDIMETHYLTAURATE COPOLYMER (4000000 MW); HYALURONATE SODIUM; HYDROGENATED SOYBEAN LECITHIN; ETHYLHEXYLGLYCERIN; MALTODEXTRIN; GLYCERYL STEARATE CITRATE; GLYCERIN; LEVOMENOL; POTASSIUM SORBATE; TOCOPHEROL; C15-19 ALKANE; POLYGLYCERIN-6; COCO-GLUCOSIDE; SODIUM BENZOATE; POLYGLYCERYL-6 LAURATE; PHENYLETHYL ALCOHOL; PENTAPEPTIDE-59

Kindra Daily V Lotion

Active ingredients

Dimethicone 2%

Purpose

Skin Protectant

Use

- helps prevent, temporarily protects, and helps relieve chafed, chapped, or cracked skin

Warnings

For external use only

When using this product do not get into eyes

Stop use and ask a doctor if

- condition worsens
- symptoms last more than 7 days or clear up and occur again within a few days

Keep out of reach of children. If swallowed, get medical help or contact a Poison Control Center right away

Directions

apply generously as needed

Inactive ingredients

Water, Glycerin, Cetearyl Alcohol, Helianthus Annuus (Sunflower) Seed Oil, Cetyl Alcohol, Coco-Glucoside, Butyrospermum Parkii (Shea) Butter, Sodium Acrylate/Sodium Acryloyldimethyl Taurate Copolymer, Sodium Hyaluronate, C15-19 Alkane, Glyceryl Stearate Citrate, Cocos Nucifera (Coconut) Oil, Lactic Acid, Bisabolol, Tocopherol, Sodium Benzoate, Potassium Sorbate, Hydrogenated Lecithin, Polyglyceryl-6 Laurate, Phenethyl Alcohol, Ethylhexylglycerin, Polyglycerin-6, Maltodextrin, Pentapeptide-59

Questions?

310-906-0242

hello@ourkindra.com

DISTR BY KINDRA

SANTA MONICA, CA 90404

Made in USA with US & imported materials

PRINCIPAL DISPLAY PANEL

KINDRA

Daily V Lotion

Hydrate and protect dry vulvovaginal skin

ESTROGEN-FREE

PATENT-PENDING FORMULA:

- Skin-calming peptide
- Shea butter
- Coconut oil

Skin Protectant

NET WT 1.0 OZ (28g)